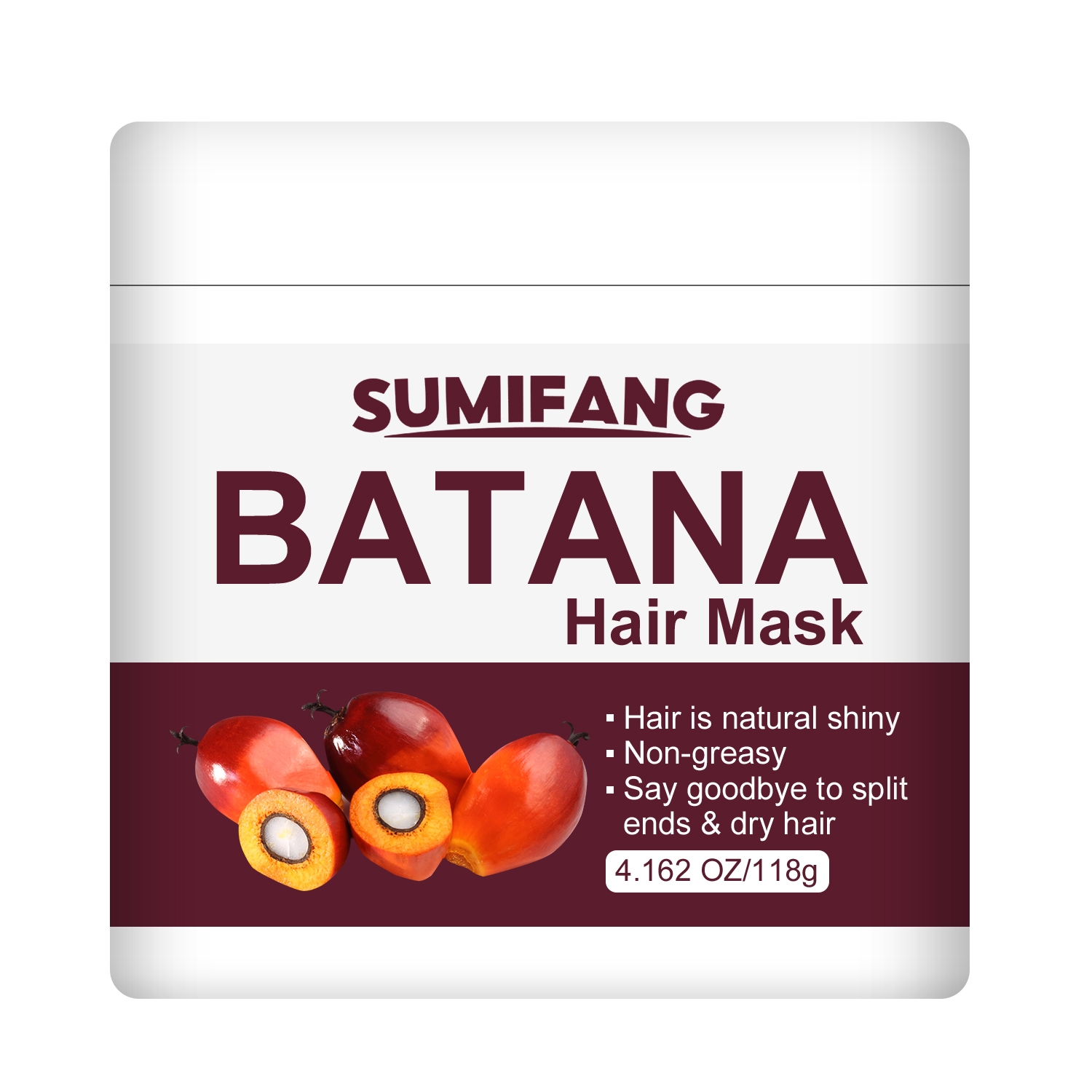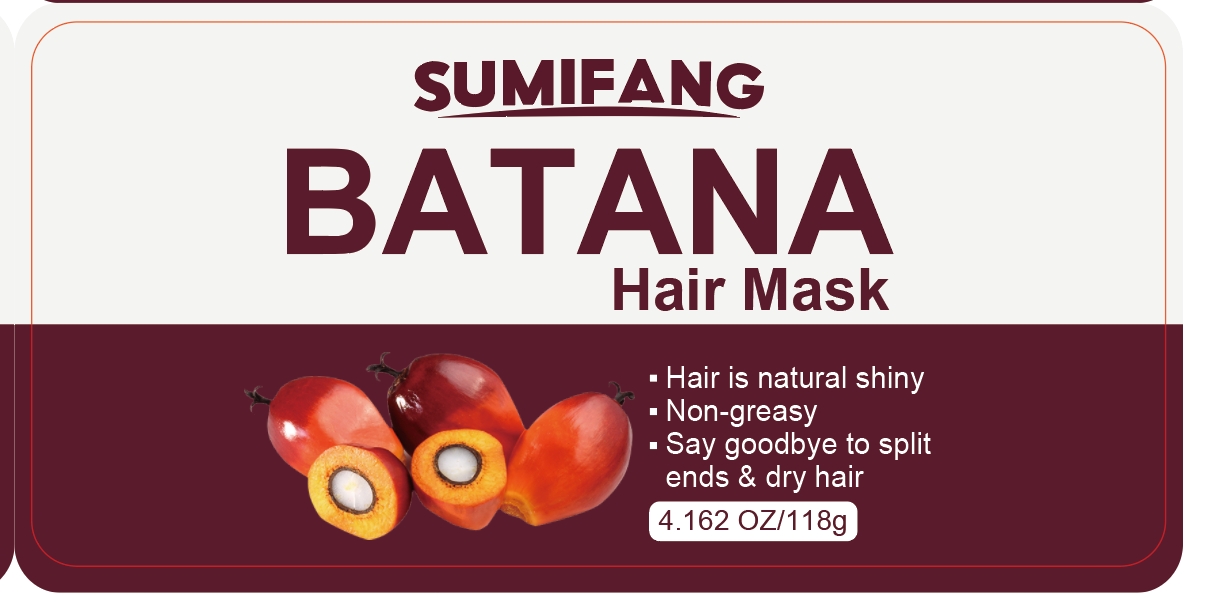 DRUG LABEL: Hairmask
NDC: 84025-121 | Form: CREAM
Manufacturer: Guangzhou Yanxi Biotechnology Co.. Ltd
Category: otc | Type: HUMAN OTC DRUG LABEL
Date: 20240806

ACTIVE INGREDIENTS: NIACINAMIDE 5 mg/118 g; CETEARYL OLIVATE 3 mg/118 g
INACTIVE INGREDIENTS: WATER

DOSAGE AND ADMINISTRATION

Hair mask for daily hair care to keep hair dry, smooth and non-greasy

WARNINGS

Keep out of children

INACTIVE INGREDIENT

Aqua

INDICATIONS AND USAGE

For daily hair care.

Keep out of children

PURPOSE

For solving the problem of dry hair and maintaining its smoothness